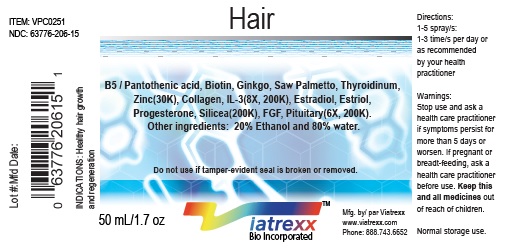 DRUG LABEL: Viatrexx-Hair
NDC: 63776-206 | Form: SPRAY
Manufacturer: VIATREXX BIO INCORPORATED
Category: homeopathic | Type: HUMAN OTC DRUG LABEL
Date: 20190319

ACTIVE INGREDIENTS: Pantothenic Acid 30 [kp_C]/1 mL; Biotin 30 [kp_C]/1 mL; Estradiol 200 [kp_C]/1 mL; Pork Collagen 200 [kp_C]/1 mL; Estriol 200 [kp_C]/1 mL; Ginkgo 30 [kp_C]/1 mL; Interleukin-3 200 [kp_C]/1 mL; Bos Taurus Pituitary Gland 200 [kp_C]/1 mL; Sus Scrofa Pituitary Gland 200 [kp_C]/1 mL; Progesterone 200 [kp_C]/1 mL; Saw Palmetto 30 [kp_C]/1 mL; Silicon Dioxide 200 [kp_C]/1 mL; Thyroid, Unspecified 30 [kp_C]/1 mL; Zinc 30 [kp_C]/1 mL; Basic Fibroblast Growth Factor (Human) 200 [kp_C]/1 mL
INACTIVE INGREDIENTS: Alcohol; Water

Hair

Active Ingredients

B5/Pantothenic acid (30K), Biotin (30K), Collagen (8X, 200K), Estradiol (200K), Estriol (200K), FGF (6X, 200K), Ginkgo (30K), IL-3 (8X, 200K), Pituitary (6X, 200K), Progesterone (200K), Saw Palmetto (30K), Silicea (200K), Thyroidium (30K), Zinc (30K).

Purpose

B5/Pantothenic acid
Biotin
Collagen
Estradiol
Estriol
FGF
Ginkgo
IL-3
Pituitary
Progesterone
Saw Palmetto
Silicea
Thyroidium
Zinc

Nutritional support
Regeneration
Regeneration
Hormonal support
Hormonal support
Regeneration
Circulation support
Immune support
Regeneration
Hormonal support
Hormonal support
Drainage
Regeneration
Nutritional support

Uses

Hair health, hair regeneration & support.

Warnings

Stop use and ask a health care practitioner if symptoms persist for more than five days or worsen. If pregnant or breastfeeding, ask a health care practitioner before use.

Dosage

1-3 spray(s); 1-3 time(s) per day or as recommended by your health care practitioner.

Inactive Ingredients

20% Alcohol and 80% Water

Other Information

Product availability

Product may be acquired in 0.5, 30, 50, 100, 250 mL in bottles

References upon request

To report SUSPECTED ADVERSE REACTIONS, contact the FDA at 1-800-FDA-1088 or www.fda.gov/medwatch

Distributed by
Viatrexx Bio Incorporated
Newark, DE, USA, 19713

Manufactured by
8046255 Canada Inc
Beloeil, Qc, J3G 6S3
Date of last revision March 2019

For Questions and comments
Info@Viatrexx.com
www.Viatrexx.com

PACKAGE LABEL.PRINCIPAL DISPLAY PANEL

NDC: 63776-206-11
Item: VPC0251
Viatrexx Bio Incorporated
Viatrexx-Hair
Box of 1 X 0.5 mL ampule
For Oral and Topical Use
Expiry date: Lot #:
Manufactured by:
Viatrexx Bio Incorporated Newark, DE, USA, 19713
www.Viatrexx.com
Ingredients, homeopathic
See insert or www.viatrexx.com
Inactives: Alcohol 20%, Water 80%

NDC: 63776-206-14
Item: VPC0251
Viatrexx Bio Incorporated
Viatrexx-Hair
Box of 1 X 30 mL spray bottle
For Oral and Topical Use
Expiry date: Lot #:
Manufactured for:
Viatrexx Bio Incorporated Newark, DE, USA, 19713
www.Viatrexx.com
Ingredients, homeopathic
See insert or www.viatrexx.com
Inactives: Alcohol 20%, Water 80%

NDC: 63776-206-15
Item: VPC0251
Viatrexx Bio Incorporated
Viatrexx-Hair
Box of 1 X 50 mL spray bottle
For Oral and Topical Use
Expiry date: Lot #:
Manufactured for:
Viatrexx Bio Incorporated Newark, DE, USA, 19713
www.Viatrexx.com
Ingredients, homeopathic
See insert or www.viatrexx.com
Inactives: Alcohol 20%, Water 80%

NDC: 63776-206-16
Item: VPC0251
Viatrexx Bio Incorporated
Viatrexx-Hair
Box of 1 X 100 mL bottle
For Oral and Topical Use
Expiry date: Lot #:
Manufactured for:
Viatrexx Bio Incorporated Newark, DE, USA, 19713
www.Viatrexx.com
Ingredients, homeopathic
See insert or www.viatrexx.com
Inactives: Alcohol 20%, Water 80%

NDC: 63776-206-17
Item: VPC0251
Viatrexx Bio Incorporated
Viatrexx-Hair
Box of 1 X 250 mL bottle
For Oral and Topical Use
Expiry date: Lot #:
Manufactured for:
Viatrexx Bio Incorporated Newark, DE, USA, 19713
www.Viatrexx.com
Ingredients, homeopathic
See insert or www.viatrexx.com
Inactives: Alcohol 20%, Water 80%